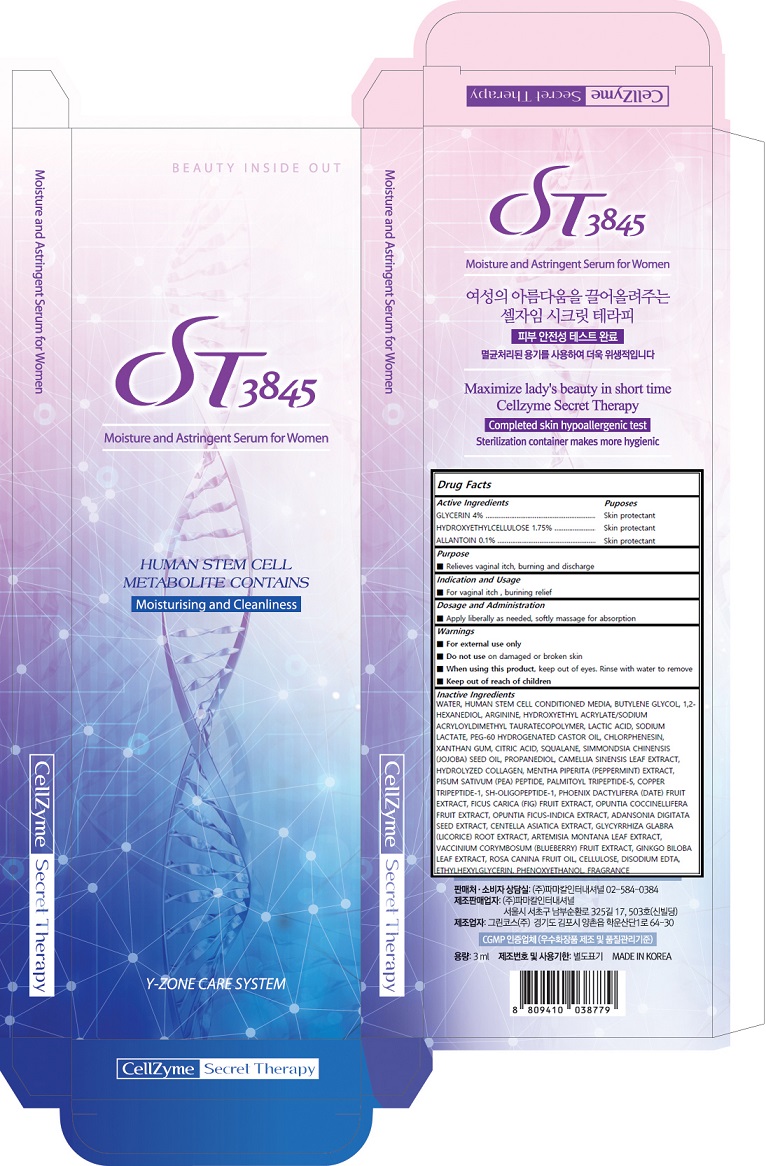 DRUG LABEL: Cellzyme Secret Therapy
NDC: 24765-109 | Form: LIQUID
Manufacturer: PHARMACAL-INTERNATIONAL. CO., LTD
Category: otc | Type: HUMAN OTC DRUG LABEL
Date: 20241025

ACTIVE INGREDIENTS: GLYCERIN 5.2 g/100 mL; HYDROXYETHYL ETHYLCELLULOSE 1.925 g/100 mL; ALLANTOIN 0.145 g/100 mL
INACTIVE INGREDIENTS: WATER; BUTYLENE GLYCOL; 1,2-HEXANEDIOL; SODIUM LACTATE; ARGININE; HYDROXYETHYL ACRYLATE/SODIUM ACRYLOYLDIMETHYL TAURATE COPOLYMER (100000 MPA.S AT 1.5%); LACTIC ACID, UNSPECIFIED FORM; PEG-60 HYDROGENATED CASTOR OIL; CHLORPHENESIN; XANTHAN GUM; CITRIC ACID MONOHYDRATE; EDETATE DISODIUM ANHYDROUS; JOJOBA OIL; SQUALANE; PROPANEDIOL; GREEN TEA LEAF; MENTHA PIPERITA; PALMITOYL TRIPEPTIDE-5; PREZATIDE COPPER; NEPIDERMIN; DATE; FIG; OPUNTIA COCHENILLIFERA FRUIT; OPUNTIA FICUS-INDICA; ADANSONIA DIGITATA SEED; CENTELLA ASIATICA; GLYCYRRHIZA GLABRA; ARTEMISIA MONTANA LEAF; GINKGO; ROSA CANINA FRUIT OIL; POWDERED CELLULOSE; ETHYLHEXYLGLYCERIN; PHENOXYETHANOL

Cellzyme Secret Therapy

Actvie Ingrdients

GLYCERIN 4% ……………………………………………………. Skin protectant

HYDROXYETHYLCELLULOSE 1.75% ……………………. Skin protectant

ALLANTOIN 0.1% ……………………………………………… Skin protectant

Inactives

WATER, HUMAN STEM CELL CONDITIONED, BUTYLENE GLYCOL, GLYCERIN, 1,2-HEXANEDIOL, ARGININE, HYDROXYETHYLCELLULOSE, HYDROXYETHYL ACRYLATE/SODIUM ACRYLOYLDIMETHYL TAURATECOPOLYMER, LACTIC ACID SODIUM LACTATE, PEG-60 HYDROGENATED CASTOR OIL, CHLORPHENESIN, XANTHAN GUM, ALLANTOIN, CITRIC ACID, SQUALANE, SIMMONDSIA CHINENSIS (JOJOBA) SEED OIL, PROPANEDIOL, CAMELLIA SINENSIS LEAF EXTRACT, HYDROLYZED COLLAGEN, MENTHA PIPERITA (PEPPERMINT) EXTRACT, PISUM SATIVUM (PEA) PEPTIDE, PALMITOYL TRIPEPTIDE-5, COPPER TRIPEPTIDE-1, SH-OLIGOPEPTIDE-1, PHOENIX DACTYLIFERA (DATE) FRUIT EXTRACT, FICUS CARICA (FIG) FRUIT EXTRACT, OPUNTIA COCCINELLIFERA FRUIT EXTRACT, OPUNTIA FICUS-INDICA EXTRACT, ADANSONIA DIGITATA SEED EXTRACT, CENTELLA ASIATICA EXTRACT, GLYCYRRHIZA GLABRA (LICORICE) ROOT EXTRACT, ARTEMISIA MONTANA LEAF EXTRACT, VACCINIUM CORYMBOSUM (BLUEBERRY) FRUIT EXTRACT, GINKGO BILOBA LEAF EXTRACT, ROSA CANINA FRUIT OIL, CELLULOSE, ETHYLHEXYLGLYCERIN, PHENOXYETHANOL, FRAGRANCE

Purpose

Relives vaginal itch,burining and discharge

Indication and Usage

For vaginal itch , burining relief

Dosage and Administration

Apply liberally as nedded, softly massage for absorption

Warnings

■ For external use only

■ Do not use on damaged or broken skin

■ When using this product, keep out of eyes. Rinse with water to remove

■ Keep out of reach of children

Keep out of reach of children